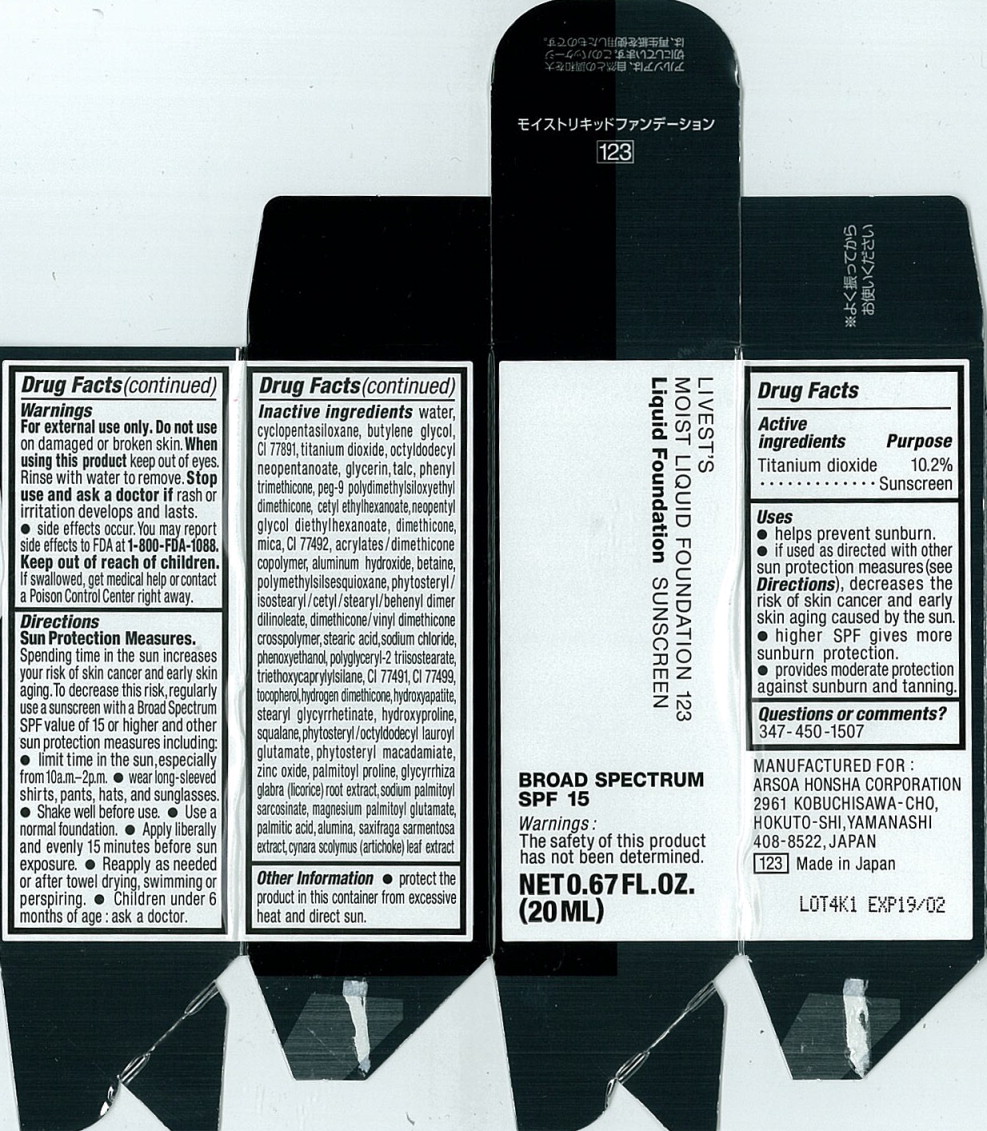 DRUG LABEL: LIVESTS MOIST FOUNDATION 123
NDC: 55655-271 | Form: LIQUID
Manufacturer: ARSOA HONSHA CORPORATION
Category: otc | Type: HUMAN OTC DRUG LABEL
Date: 20161209

ACTIVE INGREDIENTS: Titanium dioxide 2.31 g/20 mL
INACTIVE INGREDIENTS: WATER; CYCLOMETHICONE 5; BUTYLENE GLYCOL; TALC; OCTYLDODECYL NEOPENTANOATE; GLYCERIN; PHENYL TRIMETHICONE; PEG-9 POLYDIMETHYLSILOXYETHYL DIMETHICONE; CETYL ETHYLHEXANOATE; NEOPENTYL GLYCOL DIETHYLHEXANOATE; DIMETHICONE; MICA; ALUMINUM HYDROXIDE; FERRIC OXIDE YELLOW; BETAINE; PHYTOSTERYL/ISOSTEARYL/CETYL/STEARYL/BEHENYL DIMER DILINOLEATE; DIMETHICONE/VINYL DIMETHICONE CROSSPOLYMER (SOFT PARTICLE); STEARIC ACID; SODIUM CHLORIDE; PHENOXYETHANOL; POLYGLYCERYL-2 TRIISOSTEARATE; FERRIC OXIDE RED; TRIETHOXYCAPRYLYLSILANE; FERROSOFERRIC OXIDE; TOCOPHEROL; HYDROGEN DIMETHICONE (20 CST); HYDROXYPROLINE; STEARYL GLYCYRRHETINATE; SQUALANE; TRIBASIC CALCIUM PHOSPHATE; PHYTOSTERYL/OCTYLDODECYL LAUROYL GLUTAMATE; PHYTOSTERYL MACADAMIATE; ZINC OXIDE; PALMITOYL PROLINE; GLYCYRRHIZA GLABRA; SODIUM PALMITOYL SARCOSINATE; MAGNESIUM PALMITOYL GLUTAMATE; PALMITIC ACID; ALUMINUM OXIDE; SAXIFRAGA STOLONIFERA LEAF; CYNARA SCOLYMUS LEAF

Drug Facts

Active ingredients

Titanium dioxide 10.2%

Purpose

Sunscreen

Uses

- helps prevent sunburn.
- if used as directed with other sun protection measures (see Directions), decreases the risk of skin cancer and early skin aging caused by the sun.
- higher SPF gives more sunburn protection.
- provides moderate protection against sunburn and tanning.

Warnings

For external use only.

Do not use on damaged or broken skin.

When using this product keep out of eyes. Rinse with water to remove.

Stop use and ask a doctor if rash or irritation develops and lasts.

- side effects occur. You may report side effects to FDA at 1-800-FDA-1088.

Keep out of reach of children. If swallowed, get medical help or contact a Poison Control Center right away.

Directions

Sun Protection Measures.

Spending time in the sun increases your risk of skin cancer and early skin aging. To decrease this risk, regularly use a sunscreen with a Broad Spectrum SPF value of 15 or higher and other sun protection measures including:

- limit time in the sun, especially from10a.m.-2p.m.
- wear long-sleeved shirts, pants, hats, and sunglasses.
- Shake well before use.
- Use a normal foundation.
- Apply liberally and evenly 15 minutes before sun exposure.
- Reapply as needed or after towel drying, swimming or perspiring.
- Children under 6 months of age: ask a doctor.

Inactive ingredients

water, cyclopentasiloxane, butylene glycol, Cl 77891,titanium dioxide, octyldodecyl neopentanoate, glycerin, talc, phenyl trimethicone, peg-9 polydimethylsiloxyethyl dimethicone, cetyl ethylhexanoate, neopentyl glycol diethylhexanoate, dimethicone, mica, Cl 77492, acrylates/dimethicone copolymer, aluminum hydroxide, betaine, polymethylsilsesquioxane, phytosteryl/isostearyl/cetyl/stearyl/behenyl dimer dilinoleate, dimethicone/vinyl dimethicone crosspolymer, stearic acid, sodium chloride, phenoxyethanol, polyglyceryl-2 triisostearate, triethoxycaprylylsilane, Cl 77491, Cl 77499, tocopherol, hydrogen dimethicone, hydroxyapatite, stearyl glycyrrhetinate, hydroxyproline, squalane, phytosteryl/octyldodecyl lauroyl glutamate, phytosteryl macadamiate, zinc oxide, palmitoyl proline, glycyrrhiza glabra (licorice) root extract, sodium palmitoyl sarcosinate, magnesium palmitoyl glutamate, palmitic acid, alumina, saxifraga sarmentosa extract, cynara scolymus (artichoke) leaf extract

Other Information

- protect the product in this container from excessive heat and direct sun.

Principal Display Panel - 20 mL Carton Label

LIVEST'S

MOIST LIQUID FOUNDATION 123

Liqud Foundation SUNSCREEN

BROAD SPECTRUM

SPF 15

Warnings:

The safety of this product has not been determined.

NET 0.67 FL.OZ.

(20 ML)